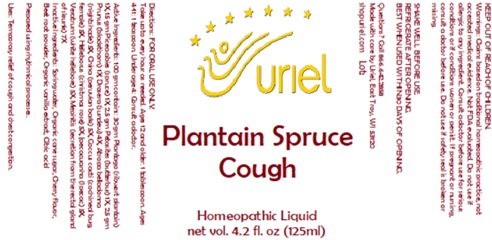 DRUG LABEL: Plantain Spruce Cough
NDC: 48951-8390 | Form: LIQUID
Manufacturer: Uriel Pharmacy Inc.
Category: homeopathic | Type: HUMAN OTC DRUG LABEL
Date: 20250107

ACTIVE INGREDIENTS: CINCHONA OFFICINALIS BARK 5 [hp_X]/1 mL; PICEA ABIES WHOLE 1 [hp_X]/1 mL; PROTORTONIA CACTI 5 [hp_X]/1 mL; IPECAC 5 [hp_X]/1 mL; PETASITES HYBRIDUS ROOT 1 [hp_X]/1 mL; SLOE 1 [hp_X]/1 mL; PLANTAGO LANCEOLATA WHOLE 1 [hp_X]/1 mL; MEPHITIS MEPHITIS ANAL GLAND FLUID 7 [hp_X]/1 mL; HELLEBORUS NIGER ROOT 5 [hp_X]/1 mL; VERATRUM ALBUM ROOT 5 [hp_X]/1 mL; DROSERA ROTUNDIFOLIA 4 [hp_X]/1 mL; ATROPA BELLADONNA 5 [hp_X]/1 mL
INACTIVE INGREDIENTS: CITRIC ACID MONOHYDRATE; WATER; CHERRY; BEET TOP; SUCROSE; VANILLA

Plantain Spruce Cough

INDICATIONS AND USAGE

Directions: FOR ORAL USE ONLY.

DOSAGE AND ADMINISTRATION

Take up to every hour as needed. Ages 12 and older: 1 tablespoon. Ages 4-11: 1 teaspoon. Under age 4: Consult a doctor.

ACTIVE INGREDIENT

Active Ingredients: 100 gm contains: 30 gm Plantago (Ribwort plantain) 1X, 15 gm Picea abies (Spruce) 1X,
2.5 gm Petasites (Butterbur) 1X, 2.5 gm Prunus (Blackthorn) 1X; Drosera (Sundew) 4X, Atropa belladonna (Nightshade) 5X,
China (Peruvian bark) 5X, Coccus cacti (Cochineal bug, female) 5X, Helleborus (Christmas rose) 5X, |pecacuanha (Ipecac) 5X,
Veratrum (White hellebore) 5X, Mephitis (Secretion from the rectal gland of skunk) 7X

INACTIVE INGREDIENT

Inactive Ingredients: Spring water, Organic cane sugar, Cherry flavor, Beet root powder, Distilled water, Organic vanilla extract, Citric acid

Prepared using rhythmical processes.

PURPOSE

Uses: Temporary relief of cough and chest congestion.

KEEP OUT OF REACH OF CHILDREN.

WARNINGS

Warnings: Claims based on traditional homeopathic practice, not accepted medical evidence. Not FDA evaluated.
Do not use if allergic to any ingredient. Consult a doctor before use for serious conditions or if conditions worsen or persist.
If pregnant or nursing, consult a doctor before use. Do not use if safety seal is broken or missing.

SHAKE WELL BEFORE USE. REFRIGERATE AFTER OPENING.
BEST WHEN USED WITHIN 30 DAYS OF OPENING.

Questions? Call 866.642.2858
Made with care by Uriel, East Troy, WI 53120
shopuriel.com Lot: